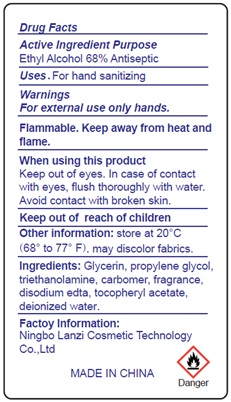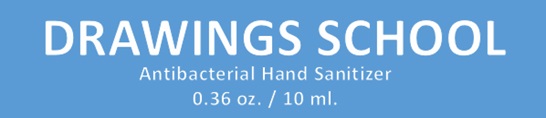 DRUG LABEL: Antibacterial hand sanitizer
NDC: 80575-000 | Form: SPRAY
Manufacturer: National Design LLC.
Category: otc | Type: HUMAN OTC DRUG LABEL
Date: 20200922

ACTIVE INGREDIENTS: ALCOHOL 0.68 mL/1 mL
INACTIVE INGREDIENTS: GLYCERIN; PROPYLENE GLYCOL; TROLAMINE; CARBOMER HOMOPOLYMER, UNSPECIFIED TYPE; EDETATE DISODIUM ANHYDROUS; .ALPHA.-TOCOPHEROL ACETATE; WATER

Antibacterial hand sanitizer

Active ingredient

Ethyl Alcohol 68%

Purpose

Antiseptic

Uses

- For hand sanitizing

Warnings

For external use only hands.

Flammable. Keep away from heat or flame.

When using this product

Keep out of eyes. In case of contact with eyes, flush thoroughly with water. Avoid contact with broken skin.

Other information:

store at 20°C (68° to 77° F). may discolor fabrics.

Ingreidients:

Glycerin, propylene glycol, triethanolamine, carbomer, fragrance, disodium edta, tocopheryl acetate, deionized water.